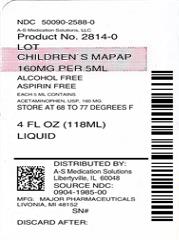 DRUG LABEL: Childrens MAPAP
NDC: 50090-2588 | Form: LIQUID
Manufacturer: A-S Medication Solutions
Category: otc | Type: HUMAN OTC DRUG LABEL
Date: 20200217

ACTIVE INGREDIENTS: ACETAMINOPHEN 160 mg/5 mL
INACTIVE INGREDIENTS: GLYCERIN; SORBITOL; SODIUM BENZOATE; ANHYDROUS CITRIC ACID; FD&C RED NO. 40; WATER; SACCHARIN SODIUM; PROPYLENE GLYCOL; PRUNUS SEROTINA BARK; POLYETHYLENE GLYCOL 1450; D&C RED NO. 33

Children's Māpap® ACETAMINOPHEN LIQUID

Drug Facts

Active ingredient (in each 5mL)

Acetaminophen 160 mg

Purpose

Pain reliever - Fever reducer

Uses

Temporarily relieves minor aches and pains due to:

- the common cold
- flu
- headache
- sore throat
- toothache

Temporarily reduces fever

Warnings

Liver warning

This product contains acetaminophen. Severe liver damage may occur if your child takes:

- more than 5 doses in 24 hours, which is the maximum daily amount
- with other drugs containing acetaminophen

Allergy alert: acetaminophen may cause severe skin reactions. Symptoms may include:

- skin reddening
- blisters
- rash

If a skin reaction occurs, stop use and seek medical help right away.

Sore throat warning

If sore throat is severe, persists for more than 2 days, is accompanied or followed by fever, headache, rash, nausea, or vomiting, consult a doctor promptly.

Do not use

- with any other product containing acetaminophen (prescription or nonprescription). If you are not sure whether a drug contains acetaminophen, ask a doctor or pharmacist
- if your child is allergic to acetaminophen or any of the inactive ingredients in this product

Ask a doctor before use if your child has liver disease

Ask a doctor or pharmacist before use if your child is taking the blood thinning drug warfarin.

When using this product, do not exceed recommended dose (see overdose warning)

Stop use and ask a doctor if

- pain gets worse or last for more than 5 days
- fever gets worse or last for more than 3 days
- new symptoms occur
- redness or swelling is present

These could be signs of a serious condition.

Keep out of the reach of children.

Overdose warning

Taking more than the recommended dose (overdose) may cause liver damage. In case of overdose, get medical help or contact a Poison Control Center (1-800-222-1222) right away. Quick medical attention is critical for adults as well as children even if you do not notice any signs or symptoms.

Directions

- this product does not contain directions or complete warnings for adult use
- find right dose on chart. If possible, use weight to dose; otherwise, use age
- mL = millileter
- if needed, repeat dose every 4 hours
- do not use more than 5 doses in 24 hours
- use enclosed dosing cup only. Do not use any other device

Weight | Age | Dose
under 24 lbs | Under 2 years | ask a doctor
24 to 35 lbs | 2 to 3 years | 5mL
36 to 47 lbs | 4 to 5 years | 7.5mL
48 to 59 lbs | 6 to 8 years | 10mL
60 to 71 lbs | 9 to 10 years | 12.5mL
72 to 95 lbs | 11 years | 15mL

Other information

- each 5 mL contains: sodium 1mg
- TAMPER-EVIDENT: Do not use this product if inner foil seal over mouth of the bottle is cut, torn, broken, or missing.
- store at 20° - 25°C (68° - 77°F)
- this product is not the same concentration as Infants' Drops. For accurate dosing, follow the dosing instructions on this label.

Inactive ingredients

artificial flavor, citric acid anhydrous, D&C Red #33, FD&C Red #40, glycerin, polyethylene glycol 1450, propylene glycol, purified water, saccharin sodium, sodium benzoate, sorbitol

Questions or Comments?

Call 1-800-616-2471

HOW SUPPLIED

Product: 50090-2588

NDC: 50090-2588-0 118 mL in a BOTTLE